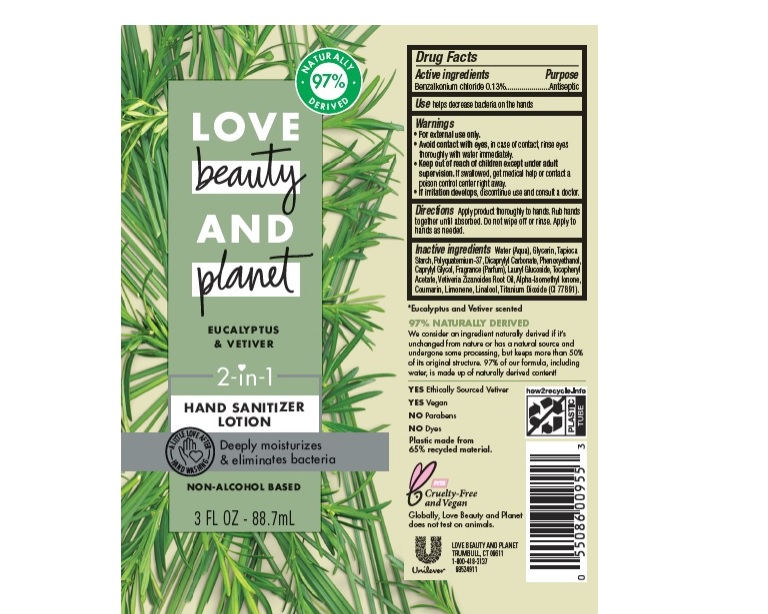 DRUG LABEL: Love Beauty and Planet
NDC: 64942-1851 | Form: LOTION
Manufacturer: Conopco Inc. d/b/a/ Unilever
Category: otc | Type: HUMAN OTC DRUG LABEL
Date: 20241107

ACTIVE INGREDIENTS: BENZALKONIUM CHLORIDE 1.3 mg/1 mL
INACTIVE INGREDIENTS: VETIVER OIL; ISOMETHYL-.ALPHA.-IONONE; COUMARIN; STARCH, TAPIOCA; POLYQUATERNIUM-37 (10000 MPA.S); DICAPRYLYL CARBONATE; WATER; GLYCERIN; CAPRYLYL GLYCOL; LAURYL GLUCOSIDE; TITANIUM DIOXIDE; PHENOXYETHANOL; .ALPHA.-TOCOPHEROL ACETATE; LIMONENE, (+)-; LINALOOL, (+/-)-

Love Beauty and Planet Eucalyptus & Vetiver Hand Sanitizer Lotion

LOVE BEAUTY AND PLANET EUCALYPTUS & VETIVER HAND SANITIZER LOTION - Benzalkonium Chloride lotion

Love Beauty and Planet Eucalyptus & Vetiver Hand Sanitizer Lotion

Drug Facts

Active ingredient

Benzalkonium Chloride 0.13%

Purpose

Antiseptic

Uses

helps decrease bacteria on the hands

Warnings

For external use only
Avoid contact with eyes, In case of contact, rinse eyes thoroughly with water.
If irritation develops, discontinue use and consult a doctor .

.

• Keep out of reach of children except under adult supervision.

If swallowed, get medical help or contact a poison control Center right away.

Directions

Apply product thoroughly to hands. Rub hands together until absorbed. Do not wipe off or rinse. Apply to hands as needed.

Inactive ingredients

Water (Aqua), Glycerin, Tapioca Starch, Polyquaternium-37, Dicaprylyl Carbonate, Phenoxyethanol, Caprylyl Glycol, Fragrance (Parfum), Lauryl Glucoside, Tocopheryl Acetate, Vetiveria Zizanoides Root Oil, Alpha-Isomethyl Ionone, Coumarin, Limonene, Linalool, Titanium Dioxide (CI 77891).

Call

1-800-418-3137